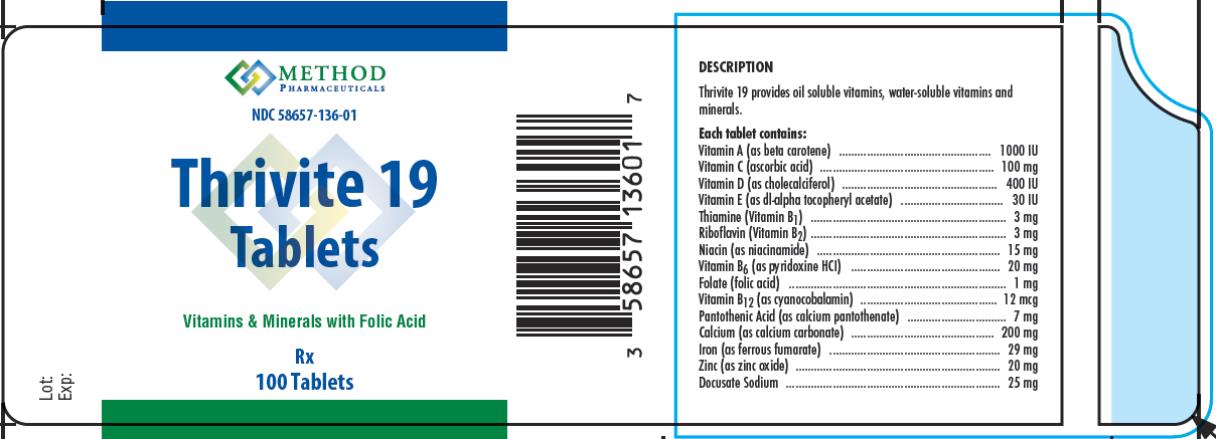 DRUG LABEL: Thrivite 19
NDC: 58657-136 | Form: TABLET, COATED
Manufacturer: Method Pharmaceuticals, LLC
Category: other | Type: DIETARY SUPPLEMENT
Date: 20150801

ACTIVE INGREDIENTS: .BETA.-CAROTENE 1000 [iU]/1 1; ASCORBIC ACID 100 mg/1 1; CHOLECALCIFEROL 400 [iU]/1 1; .ALPHA.-TOCOPHEROL ACETATE, DL- 30 [iU]/1 1; THIAMINE 3 mg/1 1; RIBOFLAVIN 3 mg/1 1; NIACINAMIDE 15 mg/1 1; PYRIDOXINE HYDROCHLORIDE 20 mg/1 1; FOLIC ACID 1 mg/1 1; CYANOCOBALAMIN 12 ug/1 1; CALCIUM PANTOTHENATE 7 mg/1 1; CALCIUM CARBONATE 200 mg/1 1; FERROUS FUMARATE 29 mg/1 1; ZINC OXIDE 20 mg/1 1; DOCUSATE SODIUM 25 mg/1 1
INACTIVE INGREDIENTS: CELLULOSE, MICROCRYSTALLINE; HYPROMELLOSES; TITANIUM DIOXIDE; POLYVINYL ALCOHOL; POLYETHYLENE GLYCOLS; TALC; CROSCARMELLOSE SODIUM; SILICON DIOXIDE; STEARIC ACID; MAGNESIUM STEARATE; ACACIA

Thrivite 19 Tablets

STATEMENT OF IDENTITY:

Thrivite 19 is an orally administered prescription dietary supplement and should be administered under the supervision of a licensed medical practitioner.

WARNING:

Accidental overdose of iron-containing products is a leading cause of fatal poisoning in children under 6. Keep this product out of reach of children. In case of accidental overdose, call a doctor or poison control center immediately.

DOSAGE AND ADMINISTRATION:

One or two tablets daily, in divided doses, or as directed by a physician.

Each tablet contains:

Vitamin A (as beta carotene) ................................................. 1000 IU

Vitamin C (ascorbic acid) ........................................................ 100 mg

Vitamin D (as cholecalciferol) .................................................. 400 IU

Vitamin E (as dl-alpha tocopheryl acetate) ................................. 30 IU

Thiamine (Vitamin B1) ............................................................... 3 mg

Riboflavin (Vitamin B2) ............................................................... 3 mg

Niacin (as niacinamide) ........................................................... 15 mg

Vitamin B6 (as pyridoxine HCI) ................................................ 20 mg

Folate (folic acid) ...................................................................... 1 mg

Vitamin B12 (as cyanocobalamin) ............................................ 12 mcg

Pantothenic Acid (as calcium pantothenate) ................................ 7 mg

Calcium (as calcium carbonate) .............................................. 200 mg

Iron (as ferrous fumarate) ....................................................... 29 mg

Zinc (as zinc oxide) .................................................................. 20 mg

Docusate Sodium ..................................................................... 25 mg

ALSO CONTAINS: Microcrystalline Cellulose, Pregelatinized Starch, Coating (Hypromellose, Titanium Dioxide, Polyvinyl Alcohol, Polyethylene Glycol, Talc), Croscarmellose Sodium, Magnesium Stearate, Stearic Acid, Fumed Silica.

HOW SUPPLIED:

Thrivite 19 tablets for oral administration are supplied as white, coated, oblong tablets debossed "M136", packaged in bottles of 100 tablets.

PRECAUTIONS/WARNING:

Folic acid alone is improper therapy in the treatment of pernicious anemia and other megaloblastic anemias where vitamin B12 is deficient. Folic acid in doses above 1 mg daily may obscure pernicious anemia in that hematologic remission can occur while neurological manifestations progress.

STORAGE: Store at 20°-25° C (68°-77° F). Excursions permitted to 15°-30° C (59°-86° F). [See USP Controlled

Room Temperature]. Protect from light and moisture. Dispense in a tight, light-resistant container.

HEALTH CLAIMS:

Prescription Vitamin B9 Containing Dietary Supplement

PRINCIPAL DISPLAY PANEL

NDC 58657-136-01
Thrivite 19
Tablets
Rx
100 Tablets